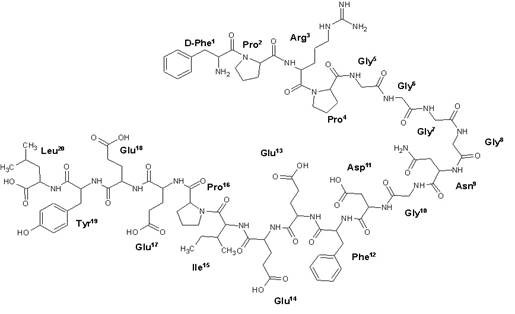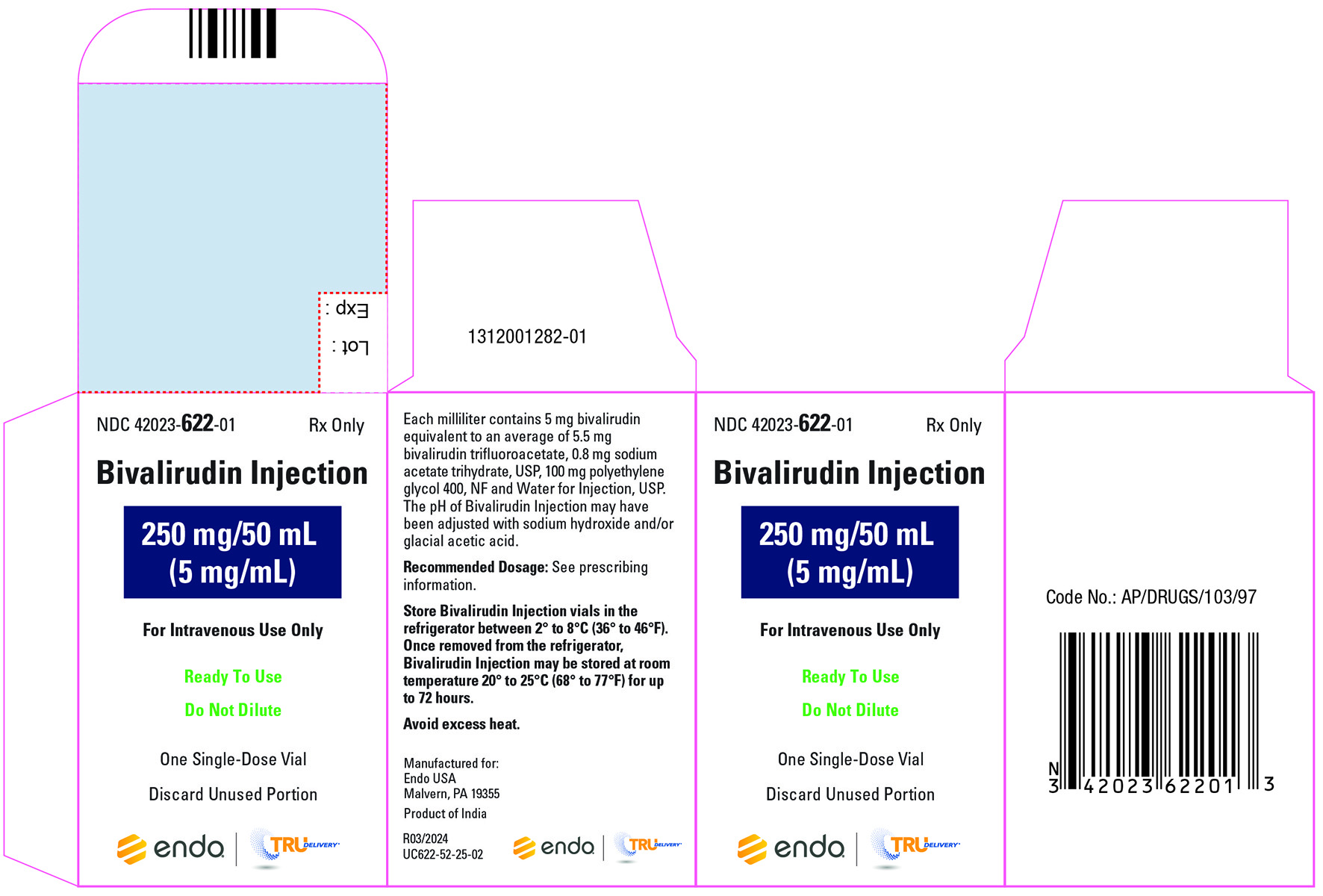 DRUG LABEL: Bivalirudin
NDC: 42023-622 | Form: INJECTION, SOLUTION
Manufacturer: Endo USA, Inc.
Category: prescription | Type: HUMAN PRESCRIPTION DRUG LABEL
Date: 20241029

ACTIVE INGREDIENTS: BIVALIRUDIN 250 mg/1 1
INACTIVE INGREDIENTS: POLYETHYLENE GLYCOL 400 5 g/1 1; SODIUM ACETATE 40 mg/1 1; WATER; SODIUM HYDROXIDE; HYDROCHLORIC ACID; ACETIC ACID

HIGHLIGHTS OF PRESCRIBING INFORMATION

These highlights do not include all the information needed to use BIVALIRUDIN INJECTION, safely and effectively. See full prescribing information for BIVALIRUDIN INJECTION.
BIVALIRUDIN injection, for intravenous use
Initial U.S. Approval: 2000

1 INDICATIONS AND USAGE

Bivalirudin Injection is a direct thrombin inhibitor indicated for use as an anticoagulant in patients undergoing percutaneous coronary intervention (PCI), including patients with heparin-induced thrombocytopenia and heparin-induced thrombocytopenia and thrombosis syndrome. (1)

2 DOSAGE AND ADMINISTRATION

- The recommended dosage is a 0.75 mg/kg intravenous bolus dose followed immediately by a 1.75 mg/kg/h intravenous infusion for the duration of the procedure. Five minutes after the bolus dose, assess activated clotting time (ACT) to determine if an additional bolus of 0.3 mg/kg is needed. (2.1)

- Consider extending duration of infusion post-procedure up to 4 hours in patients with ST segment elevation MI (2.1)

3 DOSAGE FORMS AND STRENGTHS

Injection: 250 mg/50 mL (5 mg/mL) in a single-dose vial. Ready-to-use. (3)

4 CONTRAINDICATIONS

- Significant active bleeding (4)

- Hypersensitivity to bivalirudin or its components (4)

5 WARNINGS AND PRECAUTIONS

- Bleeding events: bivalirudin increases the risk of bleeding. Its anticoagulant effect subsides approximately one hour after discontinuation. (5.1, 6.1, 12.2)
- Thrombotic risk with coronary artery brachytherapy: An increased risk of thrombus formation, including fatal outcomes, in gamma brachytherapy. (5.2, 6.2)

6 ADVERSE REACTIONS

Most common adverse reaction was bleeding (3.7%). (6.1)

To report SUSPECTED ADVERSE REACTIONS, contact Endo at 1-800-828-9393 or FDA at 1-800-FDA-1088 or www.fda.gov/medwatch.

7 DRUG INTERACTIONS

Heparin, warfarin, thrombolytics, or GPIs: Increased major bleeding risk with concomitant use. (7)

8 USE IN SPECIFIC POPULATIONS

Geriatric patients: Increased bleeding risk possible. (8.5)

Renal impairment: Reduce infusion dose and monitor ACT. (2.2, 8.6)

FULL PRESCRIBING INFORMATION

1 INDICATIONS AND USAGE

Bivalirudin Injection is indicated for use as an anticoagulant in patients undergoing percutaneous coronary intervention (PCI), including patients with heparin-induced thrombocytopenia and heparin-induced thrombocytopenia and thrombosis syndrome.

2 DOSAGE AND ADMINISTRATION

2.1 Recommended Dosage

The recommended dose of Bivalirudin Injection is an intravenous bolus dose of 0.75 mg/kg, followed immediately by a maintenance infusion of 1.75 mg/kg/h for the duration of the procedure. Five minutes after the bolus dose has been administered, assess activated clotting time (ACT) to determine if an additional bolus of 0.3 mg/kg is needed.

Consider extending duration of infusion following PCI at 1.75 mg/kg/h for up to 4 hours post- procedure in patients with ST segment elevation MI (STEMI).

2.2 Dose Adjustment in Renal Impairment

Bolus Dose:

No reduction in the bolus dose is needed for any degree of renal impairment.

Maintenance Infusion:

In patients with creatinine clearance less than 30 mL/min (by Cockcroft Gault equation), reduce the infusion rate to 1 mg/kg/h.

In patients on hemodialysis, reduce the infusion rate to 0.25 mg/kg/h [see Use in Specific Populations (8.6), Clinical Pharmacology (12.3)].

2.3 Instructions for Administration

Bivalirudin Injection is a ready-to-use sterile solution for intravenous use only.

Inspection of Container

Parenteral drug products should be inspected visually for particulate matter and discoloration prior to administration, whenever solution and container permit.

Once removed from the refrigerator, Bivalirudin Injection may be stored at room temperature 20º to 25°C (68º to 77°F) for up to 72 hours [see How Supplied Storage and Handling (16.2)]. Discard any unused portion.

Drug Compatibilities

No incompatibilities have been observed with administration sets.

Do not administer the drugs listed in Table 1 in the same intravenous line with Bivalirudin Injection.

Table 1. Drugs Not for Administration in the Same Intravenous Line with Bivalirudin Injection

Alteplase

Amiodarone HCl

Amphotericin B

Chlorpromazine HCl

Diazepam

Dobutamine

Prochlorperazine Edisylate

Reteplase

Streptokinase

Vancomycin HCl

3 DOSAGE FORMS AND STRENGTHS

Injection, clear to slightly opalescent, colorless to yellow sterile solution:

- 250 mg of bivalirudin per 50 mL (5 mg/mL) in a single-dose vial. Ready-to-use. Each vial contains 250 mg of bivalirudin equivalent to an average of 275 mg bivalirudin trifluoroacetate*.

*The range of bivalirudin trifluoroacetate is 270 to 280 mg based on a range of trifluoroacetic acid composition of 1.7 to 2.6 equivalents.

4 CONTRAINDICATIONS

Bivalirudin Injection is contraindicated in patients with:

- Significant active bleeding;
- Hypersensitivity to Bivalirudin Injection or its components [see Adverse Reactions (6.2)].

5 WARNINGS AND PRECAUTIONS

5.1 Bleeding Events

Bivalirudin increases the risk of bleeding [see Adverse Reactions (6.1)]. Bivalirudin’s anticoagulant effect subsides approximately one hour after discontinuation [see Clinical Pharmacology (12.2)].

5.2 Thrombotic Risk with Coronary Artery Brachytherapy

An increased risk of thrombus formation, including fatal outcomes, has been associated with the use of bivalirudin in gamma brachytherapy [see Adverse Reactions (6.2)].

6 ADVERSE REACTIONS

6.1 Clinical Trials Experience

Because clinical trials are conducted under widely varying conditions, adverse reaction rates observed in the clinical trials of a drug cannot be directly compared to rates in the clinical trials of another drug and may not reflect the rates observed in practice.

In the BAT trials, 79 of the 2161 (3.7%) of subjects undergoing PCI for treatment of unstable angina and randomized to bivalirudin experienced intracranial bleeding, retroperitoneal bleeding, clinically overt bleeding with a decrease in hemoglobin greater than 3 g/dL or leading to a transfusion of greater than 2 units of blood.

Immunogenicity/Re-Exposure

As with all therapeutic proteins, there is potential for immunogenicity. The detection of antibody formation is highly dependent on the sensitivity and specificity of the assay. Additionally, the observed incidence of antibody (including neutralizing antibody) positivity in an assay may be influenced by several factors including assay methodology, sample handling, timing of sample collection, concomitant medications, and underlying disease. For these reasons, comparison of the incidence of antibodies to bivalirudin in the studies described below with the incidence of antibodies in other studies or to other products may be misleading.

In in vitro studies, bivalirudin exhibited no platelet aggregation response against sera from patients with a history of HIT/HITTS.

Among 494 subjects who received bivalirudin in clinical trials and were tested for antibodies, 2 subjects had treatment-emergent positive bivalirudin antibody tests. Neither subject demonstrated clinical evidence of allergic or anaphylactic reactions and repeat testing was not performed. Nine additional patients who had initial positive tests were negative on repeat testing.

6.2 Postmarketing Experience

Because postmarketing adverse reactions are reported voluntarily from a population of uncertain size, it is not always possible to reliably estimate their frequency or establish a causal relationship to drug exposure.

The following adverse reactions have been identified during post-approval use of bivalirudin: fatal bleeding; hypersensitivity and allergic reactions including reports of anaphylaxis; lack of anticoagulant effect; thrombus formation during PCI with and without intracoronary brachytherapy, including reports of fatal outcomes; pulmonary hemorrhage; cardiac tamponade; and INR increased.

7 DRUG INTERACTIONS

In clinical trials in patients undergoing PCI, co-administration of bivalirudin with heparin, warfarin, thrombolytics, or GPIs was associated with increased risks of major bleeding events compared to patients not receiving these concomitant medications.

8 USE IN SPECIFIC POPULATIONS

8.1 Pregnancy

Risk Summary

There are no available data on use of bivalirudin in pregnant women to inform a drug-associated risk of adverse developmental outcomes. Reproduction studies in rats and rabbits administered subcutaneously (SC) doses up to 1.6 times and 3.2 times the maximum recommended human dose (MRHD) based on body surface area (BSA), respectively, revealed no evidence of fetal harm.

All pregnancies have a background risk of birth defect, loss, or other adverse outcomes. The estimated background risk of major birth defects and miscarriage for the indicated population is unknown. In the U.S. general population, the estimated background risk of major birth defects and miscarriage in clinically recognized pregnancies is 2 to 4% and 15 to 20%, respectively.

Data

Animal Data

Reproductive studies have been performed in rats at subcutaneous doses up to 150 mg/kg/day, (1.6 times the maximum recommended human dose based on body surface area) and rabbits at subcutaneous doses up to 150 mg/kg/day (3.2 times the maximum recommended human dose based on body surface area). These studies revealed no harm to the fetus attributable to bivalirudin.

At 500 mg/kg/day subcutaneously, litter sizes and live fetuses in rats were reduced. Fetal skeletal variations were also noted. Some of these changes could be attributed to maternal toxicity observed at high doses.

8.2 Lactation

Risk Summary

It is not known whether bivalirudin is present in human milk. No data are available on the effects of bivalirudin on the breastfed child or on milk production.

8.4 Pediatric Use

The safety and effectiveness of bivalirudin in pediatric patients have not been established.

8.5 Geriatric Use

In studies of patients undergoing PCI, 44% were ≥65 years of age and 12% of patients were ≥75 years old. Elderly patients experienced more bleeding events than younger patients.

8.6 Renal Impairment

The disposition of bivalirudin was studied in PTCA patients with mild, moderate and severe renal impairment. The clearance of bivalirudin was reduced approximately 21% in patients with moderate and severe renal impairment and was reduced approximately 70% in dialysis- dependent patients [see Clinical Pharmacology (12.3)]. The infusion dose of Bivalirudin Injection may need to be reduced, and anticoagulant status monitored in patients with renal impairment [see Dosage and Administration (2.2)].

10 OVERDOSAGE

Cases of overdose of up to 10 times the recommended bolus or continuous infusion dose of bivalirudin have been reported in clinical trials and in postmarketing reports. A number of the reported overdoses were due to failure to adjust the infusion dose of bivalirudin in persons with renal dysfunction including persons on hemodialysis [see Dosage and Administration (2.2)]. Bleeding, as well as deaths due to hemorrhage, have been observed in some reports of overdose. In cases of suspected overdosage, discontinue bivalirudin immediately and monitor the patient closely for signs of bleeding. There is no known antidote to bivalirudin. Bivalirudin is hemodialyzable [see Clinical Pharmacology (12.3)].

11 DESCRIPTION

Bivalirudin Injection contains bivalirudin trifluoroacetate, which is a specific and reversible direct thrombin inhibitor. Bivalirudin trifluoroacetate is a synthetic, 20 amino acid peptide salt, with the chemical name of D-phenylalanyl-L-prolyl-L-arginyl-L-prolylglycylglycylglycylglycyl-L-asparagylglycyl-L-α-aspartyl-L-phenylalanyl-L-α-glutamyl-L-α-glutamyl-L-isoleucyl-L-prolyl-L-α-glutamyl-L-α-glutamyl-L-tyrosyl-L-leucine trifluoroacetate. Each molecule of bivalirudin trifluoroacetate contains 1.7 to 2.6 equivalents of trifluoroacetic acid. The molecular formula of bivalirudin free base is C98H138N24O33 and its molecular weight is 2180.32 Daltons (anhydrous free base peptide). The structural formula of bivalirudin free base is

Figure 1: Structural Formula of Bivalirudin

Bivalirudin Injection is supplied as a refrigerated, ready-to-use, sterile solution packaged in a 50 mL single-dose vial. Each milliliter of Bivalirudin Injection contains 5 mg bivalirudin (as trifluoroacetate salt)*, 0.8 mg sodium acetate trihydrate, 100 mg polyethylene glycol 400, and Water for Injection.

The pH of Bivalirudin Injection may have been adjusted with sodium hydroxide and/or glacial acetic acid to 5.0 to 5.5. The solution is intended for intravenous administration at room temperature (20ºC to 25°C/68ºF to 77°F).

*The range of bivalirudin trifluoroacetate is 5.4 to 5.6 mg based on a range of trifluoroacetic acid composition of 1.7 to 2.6 equivalents.

12 CLINICAL PHARMACOLOGY

12.1 Mechanism of Action

Bivalirudin directly inhibits thrombin by specifically binding both to the catalytic site and to the anion-binding exosite of circulating and clot-bound thrombin. Thrombin is a serine proteinase that plays a central role in the thrombotic process, acting to cleave fibrinogen into fibrin monomers and to activate Factor XIII to Factor XIIIa, allowing fibrin to develop a covalently cross-linked framework which stabilizes the thrombus; thrombin also activates Factors V and VIII, promoting further thrombin generation, and activates platelets, stimulating aggregation and granule release. The binding of bivalirudin to thrombin is reversible as thrombin slowly cleaves the bivalirudin-Arg3-Pro4 bond, resulting in recovery of thrombin active site functions.

12.2 Pharmacodynamics

In healthy volunteers and patients (with ≥70% vessel occlusion undergoing routine PTCA), bivalirudin exhibited dose- and concentration-dependent anticoagulant activity as evidenced by prolongation of the ACT, aPTT, PT, and TT. Intravenous administration of bivalirudin produces an immediate anticoagulant effect. Coagulation times return to baseline approximately 1 hour following cessation of bivalirudin administration. Bivalirudin also increases INR.

In 291 patients with ≥70% vessel occlusion undergoing routine PTCA, a positive correlation was observed between the dose of bivalirudin and the proportion of patients achieving ACT values of 300 sec or 350 sec. At a bivalirudin dose of 1 mg/kg intravenous bolus plus 2.5 mg/kg/h intravenous infusion (1.4 times higher than the approved dose of 1.75 mg/kg/h) for 4 hours, followed by 0.2 mg/kg/h, all patients reached maximal ACT values greater than 300 sec.

12.3 Pharmacokinetics

Bivalirudin exhibits linear pharmacokinetics following intravenous administration to patients undergoing PTCA. In these patients, a mean steady state bivalirudin concentration of 12.3 ± 1.7 mcg/mL is achieved following an intravenous bolus of 1 mg/kg and a 4-hour 2.5 mg/kg/h intravenous infusion.

Distribution

Bivalirudin does not bind to plasma proteins (except thrombin) or to red blood cells.

Elimination

Bivalirudin has a half-life of 25 minutes in PTCA patients with normal renal function. The total body clearance of bivalirudin in PTCA patients with normal renal function is 3.4 mL/min/kg.

Metabolism

Bivalirudin is metabolized by proteolytic cleavage.

Excretion

Bivalirudin undergoes glomerular filtration. Tubular secretion and tubular reabsorption are also implicated in the excretion of bivalirudin, although the extent is unknown.

Specific Populations

Patients with Renal Impairment

Total body clearance was similar for PTCA patients with normal renal function and with mild renal impairment. Clearance was reduced by 21% in patients with moderate and severe renal impairment with a half-life of 34 and 57 minutes, respectively. In dialysis patients, clearance was reduced by 70%, with a half-life of 3.5 hours. Approximately 25% bivalirudin is cleared by hemodialysis.

13 NONCLINICAL TOXICOLOGY

13.1 Carcinogenesis, Mutagenesis, Impairment of Fertility

No long-term studies in animals have been performed to evaluate the carcinogenic potential of bivalirudin. Bivalirudin displayed no genotoxic potential in the in vitro bacterial cell reverse mutation assay (Ames test), the in vitro Chinese hamster ovary cell forward gene mutation test (CHO/HGPRT), the in vitro human lymphocyte chromosomal aberration assay, the in vitro rat hepatocyte unscheduled DNA synthesis (UDS) assay, and the in vitro rat micronucleus assay. Fertility and general reproductive performance in rats were unaffected by subcutaneous doses of bivalirudin up to 150 mg/kg/day, about 1.6 times the dose on a body surface area basis (mg/m^2) of a 50 kg person given the maximum recommended dose of 15 mg/kg/day.

14 CLINICAL STUDIES

Bivalirudin Angioplasty Trial (BAT)

In the BAT studies, patients with unstable angina undergoing PCI were randomized 1:1 to a 1 mg/kg bolus of bivalirudin and then 2.5 mg/kg/h for four hours and then 0.2 mg/kg/h for 14 to 20 hours or to 175 IU/kg bolus of heparin followed by an 18- to 24-hour infusion of 15 IU/kg/h infusion. Additional heparin but not bivalirudin could be administered for ACT less than 350 seconds. The studies were designed to demonstrate the superiority of bivalirudin to heparin on the occurrence of any of the following during hospitalization up to seven days of death, MI, abrupt closure of the dilated vessel, or clinical deterioration requiring revascularization or placement of an aortic balloon pump.

The 4312 subjects ranged in age from 29 to 90 (median 63) years. 68% were male, and 91% were Caucasian. Median weight was 80 kg (39 to 120 kg). 741 (17%) subjects had post-MI angina.

Twenty-three percent of patients were treated with heparin within one hour prior to randomization.

The studies did not demonstrate that bivalirudin was statistically superior to heparin for reducing the risk of death, MI, abrupt closure of the dilated vessel, or clinical deterioration requiring revascularization or placement of an aortic balloon pump, but the occurrence of these events was similar in both treatment groups. Study outcomes are shown in Table 2.

Table 2: Incidences of In-hospital Endpoints in BAT Trial

Endpoint | Bivalirudin (n=2161) | HEPARIN (n=2151)
Primary endpoint† | 7.9% | 9.3%
Death, MI, revascularization | 6.2% | 7.9%
Death | 0.2% | 0.2%
MI | 3.3% | 4.2%

† A composite of death or MI or clinical deterioration of cardiac origin requiring revascularization or placement of an aortic balloon pump or angiographic evidence of abrupt vessel closure

AT-BAT Trial (NCT# 00043940)

This was a single-arm open-label study in which 51 subjects with heparin-induced thrombocytopenia (HIT) or heparin induced thrombocytopenia and thrombosis syndrome (HITTS) undergoing PCI. The majority of patients achieved adequate ACT at the time of device activation and no major bleeding was reported. Two patients developed thrombocytopenia.

16 HOW SUPPLIED/STORAGE AND HANDLING

16.1 How Supplied

Bivalirudin Injection is supplied as a refrigerated, ready-to-use, clear to slightly opalescent, colorless to yellow, sterile solution in 250 mg/50 mL (5 mg/mL) single-dose, glass vials. The single-dose vials are available as follows:

- NDC 42023-622-01: Carton containing 1 Bivalirudin Injection single-dose vial
- NDC 42023-622-10: Carton containing 10 Bivalirudin Injection single-dose vials

Each vial contains 250 mg of bivalirudin (equivalent to an average of 275 mg bivalirudin trifluoroacetate*).

*The range of bivalirudin trifluoroacetate is 270 to 280 mg based on a range of trifluoroacetic acid composition of 1.7 to 2.6 equivalents.

16.2 Storage

Store Bivalirudin Injection vials in the refrigerator between 2° to 8°C (36° to 46°F). Once removed from the refrigerator, Bivalirudin Injection may be stored at room temperature 20º to 25°C (68º to 77°F) for up to 72 hours [see Dosage and Administration (2.3)]. Avoid excess heat.

17 PATIENT COUNSELING INFORMATION

Advise patients to watch carefully for any signs of bleeding or bruising and to report these to their healthcare provider when they occur.

Manufactured for:

Endo USA

Malvern, PA 19355

Product of India

R03/2024